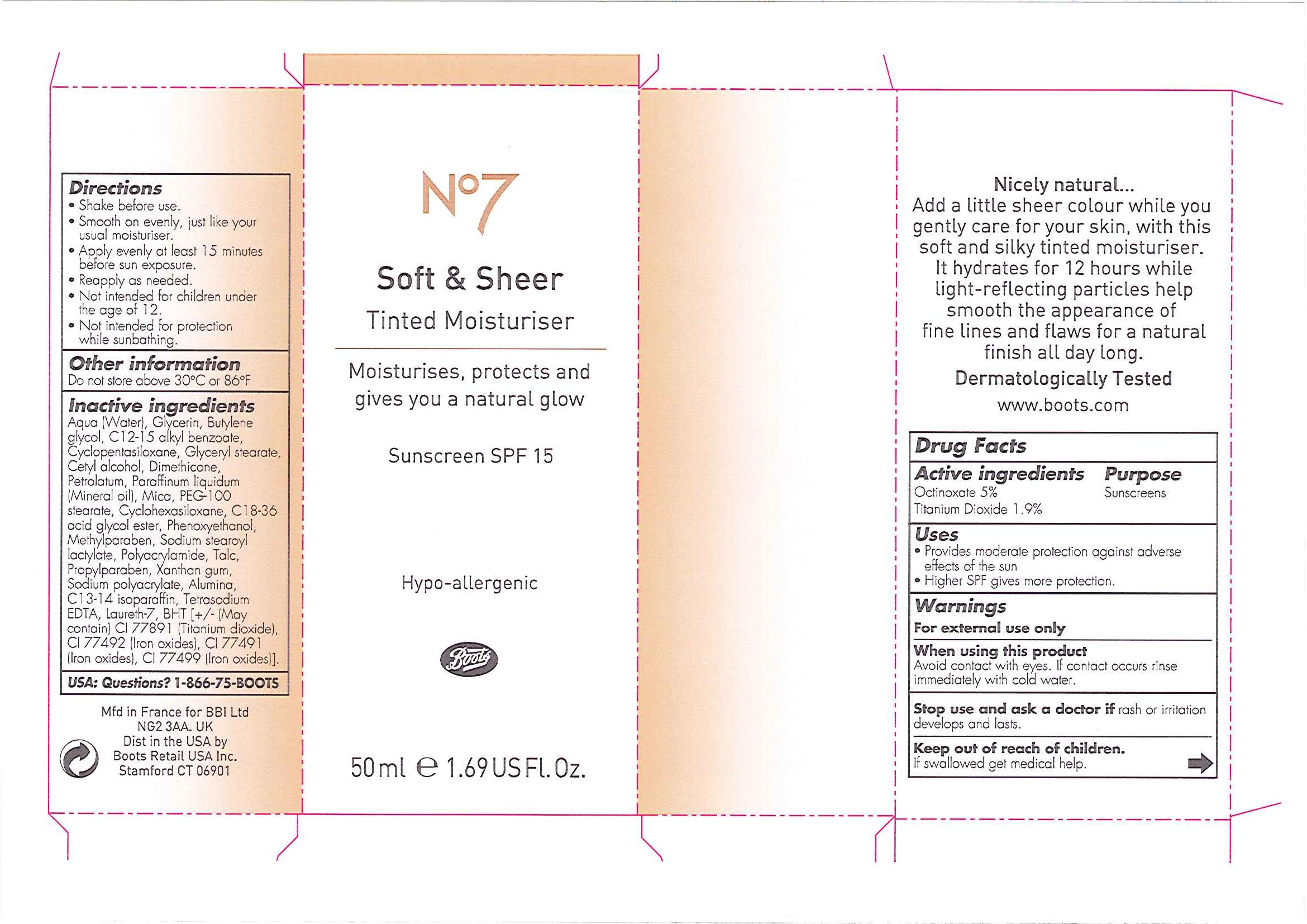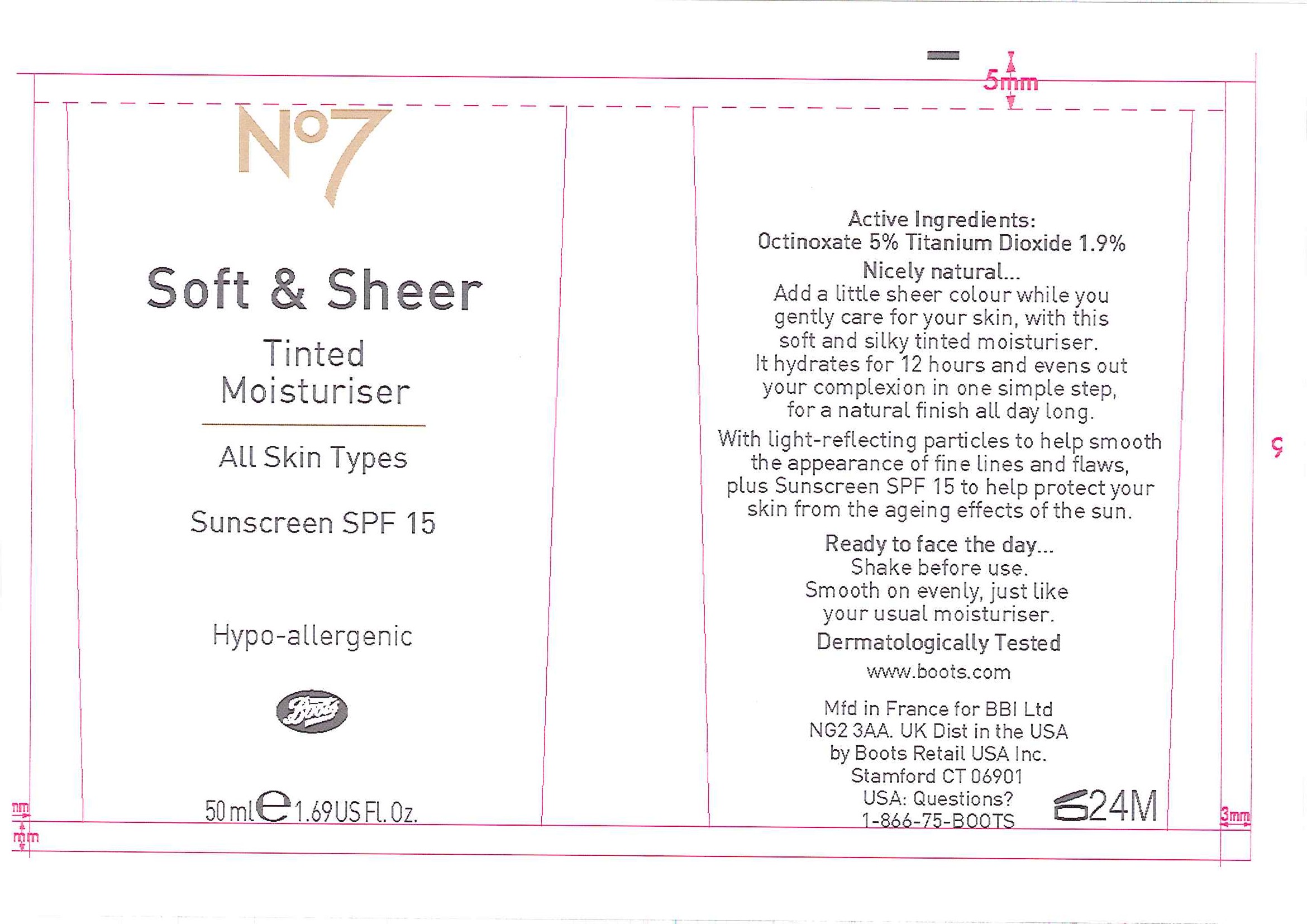 DRUG LABEL: No7 Soft and Sheer Tinted Moisturiser Dark
NDC: 61589-1906 | Form: EMULSION
Manufacturer: BCM Cosmetique SAS
Category: otc | Type: HUMAN OTC DRUG LABEL
Date: 20101206

ACTIVE INGREDIENTS: OCTINOXATE 2.5 mL/50 mL; TITANIUM DIOXIDE 0.95 mL/50 mL
INACTIVE INGREDIENTS: WATER; GLYCERIN; BUTYLENE GLYCOL; C12-15 ALKYL BENZOATE; CYCLOMETHICONE 5; GLYCERYL MONOSTEARATE; CETYL ALCOHOL; DIMETHICONE; PETROLATUM; MINERAL OIL; POLYOXYL 100 STEARATE; CYCLOMETHICONE 6; PHENOXYETHANOL; METHYLPARABEN; TALC; PROPYLPARABEN; XANTHAN GUM; ALUMINUM OXIDE; C13-14 ISOPARAFFIN; EDETATE SODIUM; BUTYLATED HYDROXYTOLUENE; FERRIC OXIDE YELLOW; FERRIC OXIDE RED; FERROSOFERRIC OXIDE

Carton and tube labelling

Active Ingredients Purpose

Octinoxate 5% Sunscreens

Titanium Dioxide 1.9%

Uses

- Provides moderate protection against adverse effects of the sun
- Higher SPF gives more protection.

Warnings

For external use only

When using this product

Avoid contact with eyes. If contact occurs rinse immediately with cold water.

Stop use and ask a doctor if rash or irritation develops and lasts.

Keep out of reach of children. If swallowed get medical help.

Directions

- Shake before use.
- Smooth on evenly, just like your usual moisturiser.
- Apply evenly at least 15 minutes before sun exposure.
- Reapply as needed.
- Not intended for children under the age of 12.
- Not intended for protection while sunbathing.

Other information

Do not store above 30^0C or 86^0F

Inactive ingredients

Aqua (Water), Glycerin, Butylene glycol, C12-15 alkyl benzoate, Cyclopentasiloxane, Glyceryl stearate, Cetyl alcohol, Dimethicone, Petrolatum, Paraffinum liquidum (Mineral oil), Mica, PEG-100 stearate, Cyclohexasiloxane, C18-36 acid glycol ester, Phenoxyethanol, Methylparaben, Sodium stearoyl lactylate, Polyacrylamide, Alumina, C13-14 isoparaffin, Tetrasodium EDTA, Laureth-7, BHT [+/- (May contain) CI 77891 (Titanium dioxide), CI 77492 (Iron oxides), CI 77491 (Iron oxides), CI 77499 (Iron oxides).

USA: Questions? 1-866-75-BOOTS

PATIENT COUNSELING INFORMATION

Mfd in France for BBI Ltd NG2 3AA. UK

Dist in the USA by Boots Retail USA Inc. Stamford CT 06901

DESCRIPTION

Nicely natural...

Add a little sheer colour while you gently care for your skin, with this soft and silky tinted moisturiser. It hydrates for 12 hours while light-reflecting particles help smooth the appearance of fine lines and flaws for a natural finish all day long.

Dermatologically Tested

www.boots.com

ACTIVE INGREDIENT

Tube label

Active Ingredients:

Octinoxate 5%

Titanium Dioxide 1.9%

DESCRIPTION

Nicely natural...

Add a little sheer colour while you gently care for your skin, with this soft and silky tinted moisturiser. It hydrates for 12 hours and evens out your complexion in one simple step, for a natural finish all day long.

With light reflecting particles to help smooth the appearance of fine lines and flaws, plus Sunscreen SPF 15 to help protect your skin from the ageing effects of the sun.

Ready to face the day...

Shake before use. Smooth on evenly, just like your usual moisturiser.

Dermatologically Tested.

PATIENT COUNSELING INFORMATION

www.boots.com

Mfd in France for BBI Ltd NG2 3AA. UK

Dist in the USA by Boots Retail USA Inc. Stamford CT 06901

USA: Questions? 1-866-75-BOOTS

PACKAGE LABEL

No7 Soft and Sheer Tinted Moisturiser

Moisturises, protects and gives you a natural glow

Sunscreen SPF 15

Hypo-allergenic

Boots

50ml e 1.69 US Fl. Oz

Soft and Sheer Tinted Moisturiser carton.jpg

PACKAGE LABEL

No7

Soft and Sheet Tinted Moisturiser

All Skin types

Sunscreen SPF 15

Hypo-allergenic

Boots

50ml e 1.69 US Fl. Oz

Soft and Sheer Tinted Moisturiser tube.jpg